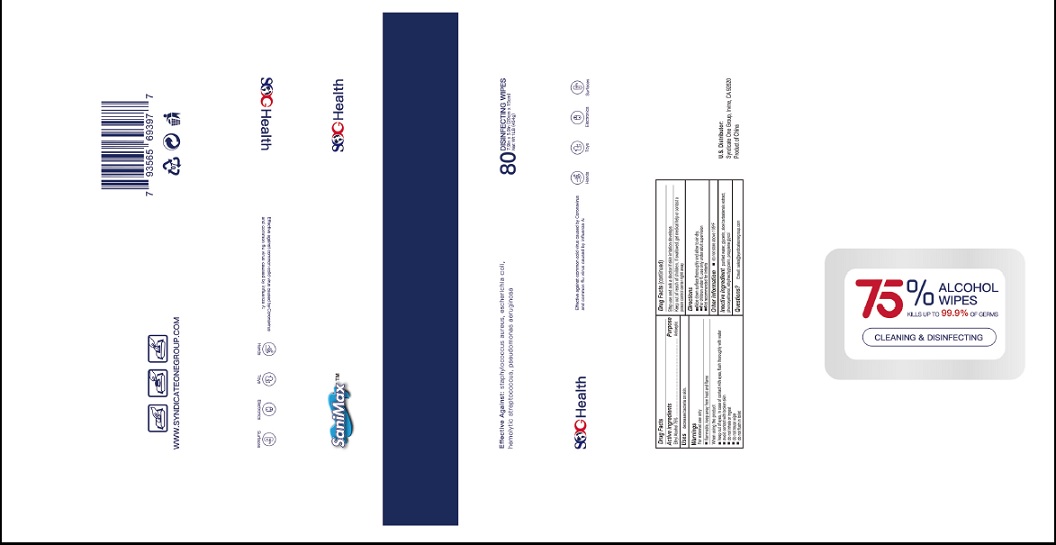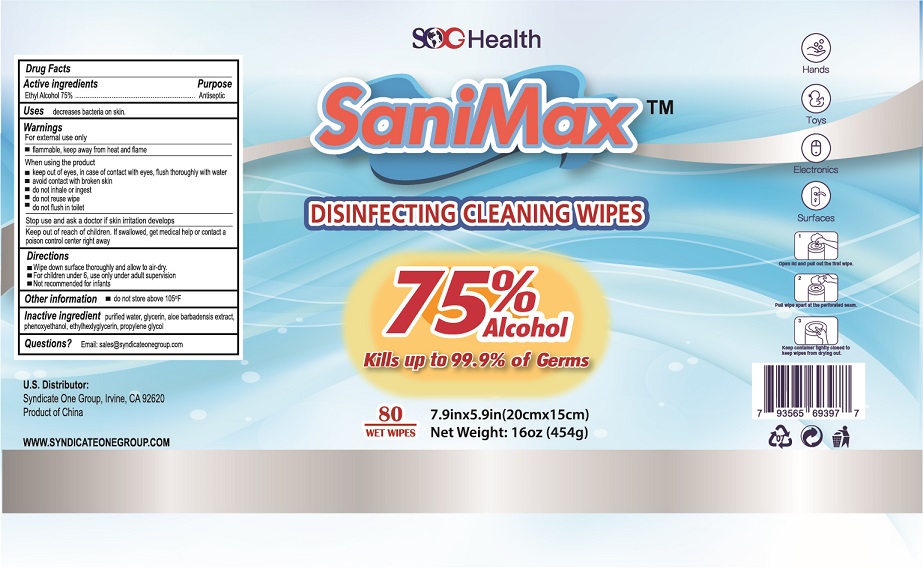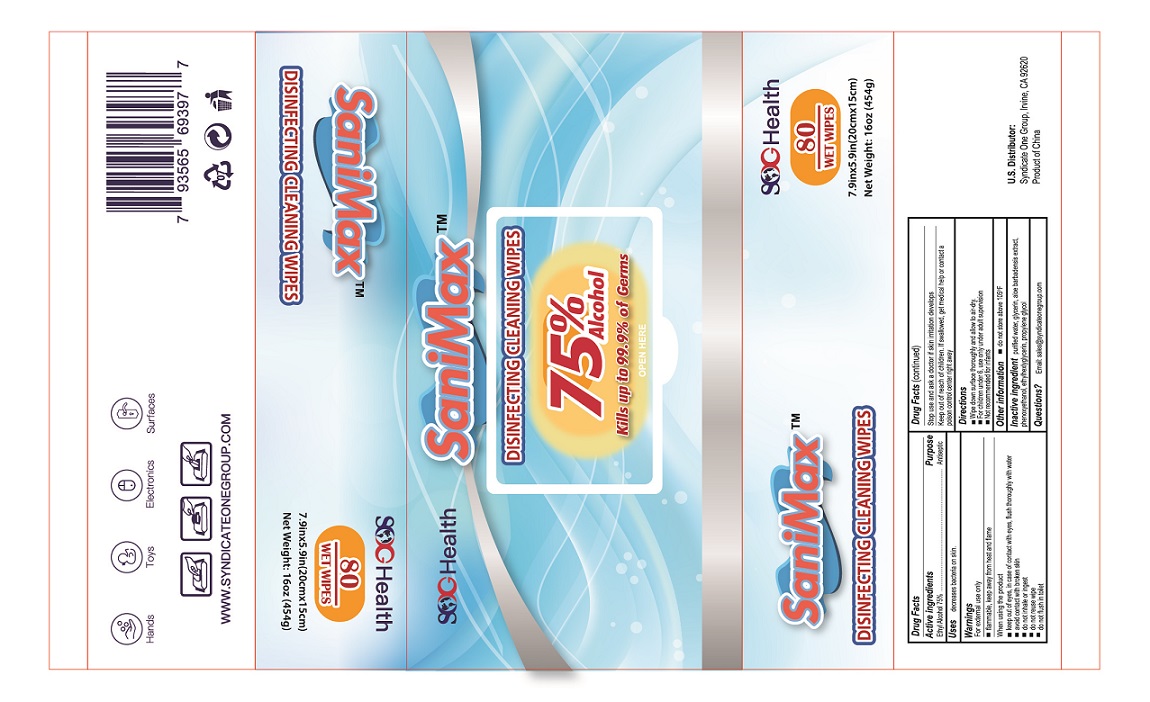 DRUG LABEL: SaniMax
NDC: 79308-001 | Form: CLOTH
Manufacturer: SYNDICATE ONE GROUP INC
Category: otc | Type: HUMAN OTC DRUG LABEL
Date: 20200626

ACTIVE INGREDIENTS: ALCOHOL 75 mL/100 mL
INACTIVE INGREDIENTS: WATER; GLYCERIN; ALOE VERA LEAF; PHENOXYETHANOL; ETHYLHEXYLGLYCERIN; PROPYLENE GLYCOL

Active Ingredient

Ethyl Alcohol 75% v/v.

Purpose

Antiseptic

Use

decreases bacteria on skin.

Warnings

For external use only.

Flammable. Keep away from heat and flame.

When using the product

- keep out of eyes, in case of contact with eyes, flush thoroughly with water
- avoid contact with broken skin
- do not inhale or ingest
- do not reuse wipe
- do not flush in toilet

Stop use and ask a doctor if skin irritation develops.

Keep out of reach of children. If swallowed, get medical help or contact a Poison Control Center right away.

Directions

- Wipe down surface thoroughly and allow to air-dry.
- For children under 6, use only under adult supervision
- Not recommended for infants

Other information

- do not store above 105°F

Inactive ingredients

purified water, glycerin. aloe barbadensis extract, phenoxyethanol, ethylhexlyglycerin, propylene glycol